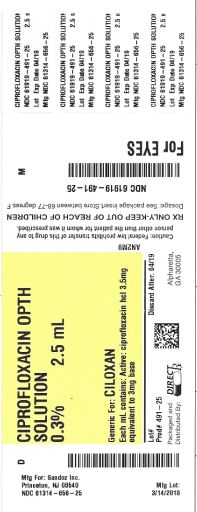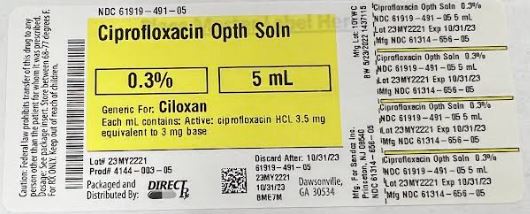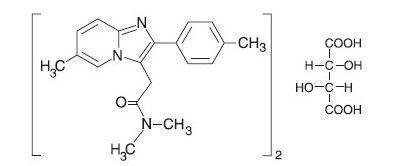 DRUG LABEL: CIPROFLOXACIN
NDC: 61919-491 | Form: SOLUTION/ DROPS
Manufacturer: DIRECT RX
Category: prescription | Type: HUMAN PRESCRIPTION DRUG LABEL
Date: 20220603

ACTIVE INGREDIENTS: CIPROFLOXACIN HYDROCHLORIDE 3 mg/1 mL
INACTIVE INGREDIENTS: BENZALKONIUM CHLORIDE; MANNITOL; EDETATE DISODIUM; SODIUM ACETATE; ACETIC ACID; WATER; SODIUM HYDROXIDE; HYDROCHLORIC ACID

CIPROFLOXACIN OPTH SOLUTION

DESCRIPTION SECTION

Ciprofloxacin Ophthalmic Solution is a synthetic, sterile, multiple dose, antimicrobial for topical use. Ciprofloxacin is a fluoroquinolone antibacterial active against a broad spectrum of gram positive and gram-negative ocular pathogens. It is available as the monohydrochloride monohydrate salt of 1-cyclopropyl-6-fluoro-1,4-dihydro-4-oxo-7-(1-piperazinyl)-3-quinoline-carboxylic acid. It is a faint to light yellow crystalline powder with a molecular weight of 385.8. Its empirical formula is C17H18FN3O3•HCl•H2O and its chemical structure is as follows:

Ciprofloxacin differs from other quinolones in that it has a fluorine atom at the 6-position, a piperazine moiety at the 7-position, and a cyclopropyl ring at the 1-position.

Each mL of Ciprofloxacin Ophthalmic Solution contains: Active: Ciprofloxacin HCl 3.5 mg equivalent to 3 mg base. Preservative: benzalkonium chloride 0.006%. Inactives: sodium acetate, acetic acid, mannitol 4.6%, edetate disodium 0.05%, hydrochloric acid and/or sodium hydroxide (to adjust pH) and Water for Injection. The pH is approximately 4.5 and the osmolality is approximately 300 mOsm.

CLINICAL PHARMACOLOGY SECTION

Systemic Absorption: A systemic absorption study was performed in which Ciprofloxacin Ophthalmic Solution was administered in each eye every two hours while awake for two days followed by every four hours while awake for an additional 5 days. The maximum reported plasma concentration of ciprofloxacin was less than 5 ng/mL. The mean concentration was usually less than 2.5 ng/mL.

Microbiology: Ciprofloxacin has in vitro activity against a wide range of gram-negative and gram-positive organisms. The bactericidal action of ciprofloxacin results from interference with the enzyme DNA gyrase which is needed for the synthesis of bacterial DNA. Ciprofloxacin has been shown to be active against most strains of the following microorganisms both in vitro and in clinical infections (SEE INDICATIONS AND USAGE section):

Gram-Positive:

Staphylococcus aureus

Staphylococcus epidermidis

Streptococcus pneumoniae

Streptococcus (Viridans Group)

Gram-Negative:

Haemophilus influenzae

Pseudomonas aeruginosa

Serratia marcescens

Ciprofloxacin has been shown to be active in vitro against most strains of the following organisms, however, the clinical significance of these data is unknown:

Gram-Positive:

Enterococcus faecalis (Many strains are only moderately susceptible)

Staphylococcus haemolyticus

Staphylococcus hominis

Staphylococcus saprophyticus

Streptococcus pyogenes

Gram-Negative

Acinetobacter calcoaceticus Escherichia coli Proteus mirabilis

subsp. anitratus Haemophilus ducreyi Proteus vulgaris

Aeromonas caviae Haemophilus parainfluenzae Providencia rettgeri

Aeromonas hydrophila Kiebsiella pneumoniae Providencia stuartii

Brucella melitensis Kiebsiella oxytoca Salmonella enteritidis

Campylobacter coli Legionella pneumophila Salmonella typhi

Campylobacter jejuni Moraxella (Branhamella) Shigella sonneii

Citrobacter diversus catarrhalis Shigella flexneri

Citrobacter freundii Morganella morganii Vibrio cholerae

Edwardsiella tarda Neisseria gonorrhoeae Vibrio parahaemolyticus

Enterobacter aerogenes Neisseria meningitidis Vibrio vulnificus

Enterobacter cloacae Pasteurella multocida Yersinia enterocolitica

Other Organisms: Chlamydia trachomatis (only moderately susceptible) and Mycobacterium tuberculosis (only moderately susceptible).

Most strains of Pseudomonas cepacia and some strains of Pseudomonas maltophilia are resistant to ciprofloxacin as are most anaerobic bacteria, including Bacteroides fragilis and Clostridium difficile. The minimal bactericidal concentration (MBC) generally does not exceed the minimal inhibitory concentration (MIC) by more than a factor of 2. Resistance to ciprofloxacin in vitro usually develops slowly (multiple-step mutation).

Ciprofloxacin does not cross-react with other antimicrobial agents such as beta-lactams or aminoglycosides; therefore, organisms resistant to these drugs may be susceptible to ciprofloxacin.

Clinical Studies: Following therapy with Ciprofloxacin Ophthalmic Solution, 76% of the patients with corneal ulcers and positive bacterial cultures were clinically cured and complete re-epithelialization occurred in about 92% of the ulcers. In 3 and 7 day multicenter clinical trials, 52% of the patients with conjunctivitis and positive conjunctival cultures were clinically cured and 70-80% had all causative pathogens eradicated by the end of treatment.

INDICATIONS & USAGE SECTION

Ciprofloxacin Ophthalmic Solution is indicated for the treatment of infections caused by susceptible strains of the designated microorganisms in the conditions listed below:

Corneal Ulcers: Pseudomonas aeruginosa

Serratia marcescens *

Staphylococcus aureus

Staphylococcus epidermidis

Streptococcus pneumoniae

Streptococcus (Viridans Group) *

Conjunctivitis: Haemophilus influenzae

Staphylococcus aureus

Staphylococcus epidermidis

Streptococcus pneumoniae

* Efficacy for this organism was studied in fewer than 10 infections.

CONTRAINDICATIONS SECTION

A history of hypersensitivity to ciprofloxacin or any other component of the medication is a contraindication to its use. A history of hypersensitivity to other quinolones may also contraindicate the use of ciprofloxacin.

WARNINGS SECTION

NOT FOR INJECTION INTO THE EYE.

Serious and occasionally fatal hypersensitivity (anaphylactic) reactions, some following the first dose, have been reported in patients receiving systemic quinolone therapy. Some reactions were accompanied by cardiovascular collapse, loss of consciousness, tingling, pharyngeal or facial edema, dyspnea, urticaria, and itching. Only a few patients had a history of hypersensitivity reactions. Serious anaphylactic reactions require immediate emergency treatment with epinephrine and other resuscitation measures, including oxygen, intravenous fluids, intravenous antihistamines, corticosteroids, pressor amines and airway management, as clinically indicated. Remove contact lenses before using.

PRECAUTIONS SECTION

General: As with other antibacterial preparations, prolonged use of ciprofloxacin may result in overgrowth of nonsusceptible organisms, including fungi. If superinfection occurs, appropriate therapy should be initiated. Whenever clinical judgment dictates, the patient should be examined with the aid of magnification, such as slit lamp biomicroscopy and, where appropriate, fluorescein staining. Ciprofloxacin should be discontinued at the first appearance of a skin rash or any other sign of hypersensitivity reaction. In clinical studies of patients with bacterial corneal ulcer, a white crystalline precipitate located in the superficial portion of the corneal defect was observed in 35 (16.6%) of 210 patients. The onset of the precipitate was within 24 hours to 7 days after starting therapy. In one patient, the precipitate was immediately irrigated out upon its appearance. In 17 patients, resolution of the precipitate was seen in 1 to 8 days (seven within the first 24-72 hours), in five patients, resolution was noted in 10-13 days. In nine patients, exact resolution days were unavailable; however, at follow-up examinations, 18-44 days after onset of the event, complete resolution of the precipitate was noted. In three patients, outcome information was unavailable. The precipitate did not preclude continued use of ciprofloxacin, nor did it adversely affect the clinical course of the ulcer or visual outcome. (SEE ADVERSE REACTIONS).

Information for patients: Do not touch dropper tip to any surface, as this may contaminate the solution.

Drug Interactions: Specific drug interaction studies have not been conducted with ophthalmic ciprofloxacin. However, the systemic administration of some quinolones has been shown to elevate plasma concentrations of theophylline, interfere with the metabolism of caffeine, enhance the effects of the oral anticoagulant, warfarin, and its derivatives, and has been associated with transient elevations in serum creatinine in patients receiving cyclosporine concomitantly.

Carcinogenesis, Mutagenesis, Impairment of Fertility:

Eight in vitro mutagenicity tests have been conducted with ciprofloxacin and the test results are listed below:

Salmonella/Microsome Test (Negative)

E. coli DNA Repair Assay (Negative)

Mouse Lymphoma Cell Forward Mutation Assay (Positive)

Chinese Hamster V79 Cell HGPRT Test (Negative)

Syrian Hamster Embryo Cell Transformation Assay (Negative)

Saccharomyces cerevisiae Point Mutation Assay (Negative)

Saccharomyces cerevisiae Mitotic Crossover and Gene Conversion Assay (Negative)

Rat Hepatocyte DNA Repair Assay (Positive)

Thus, two of the eight tests were positive, but the results of the following three in vivo test systems gave negative results:

Rat Hepatocyte DNA Repair Assay

Micronucleus Test (Mice)

Dominant Lethal Test (Mice).

Long term carcinogenicity studies in mice and rats have been completed. After daily oral dosing for up to two years, there is no evidence that ciprofloxacin had any carcinogenic or tumorigenic effects in these species.

Pregnancy: Pregnancy Category C. Reproduction studies have been performed in rats and mice at doses up to six times the usual daily human oral dose and have revealed no evidence of impaired fertility or harm to the fetus due to ciprofloxacin. In rabbits, as with most antimicrobial agents, ciprofloxacin (30 and 100 mg/kg orally) produced gastrointestinal disturbances resulting in maternal weight loss and an increased incidence of abortion. No teratogenicity was observed at either dose. After intravenous administration, at doses up to 20 mg/kg, no maternal toxicity was produced and no embryotoxicity or teratogenicity was observed. There are no adequate and well controlled studies in pregnant women. Ciprofloxacin Ophthalmic Solution should be used during pregnancy only if the potential benefit justifies the potential risk to the fetus.

Nursing Mothers: It is not known whether topically applied ciprofloxacin is excreted in human milk. However, it is known that orally administered ciprofloxacin is excreted in the milk of lactating rats and oral ciprofloxacin has been reported in human breast milk after a single 500 mg dose. Caution should be exercised when Ciprofloxacin Ophthalmic Solution is administered to a nursing mother.

Pediatric Use: Safety and effectiveness in pediatric patients below the age of 1 year have not been established. Although ciprofloxacin and other quinolones cause arthropathy in immature animals after oral administration, topical ocular administration of ciprofloxacin to immature animals did not cause any arthropathy and there is no evidence that the ophthalmic dosage form has any effect on the weight bearing joints.

Geriatric Use: No overall differences in safety or effectiveness have been observed between elderly and younger patients.

ADVERSE REACTIONS SECTION

The most frequently reported drug related adverse reaction was local burning or discomfort. In corneal ulcer studies with frequent administration of the drug, white crystalline precipitates were seen in approximately 17% of patients (SEE PRECAUTIONS). Other reactions occurring in less than 10% of patients included lid margin crusting, crystals/scales, foreign body sensation, itching, conjunctival hyperemia and a bad taste following instillation. Additional events occurring in less than 1% of patients included corneal staining, keratopathy/keratitis, allergic reactions, lid edema, tearing, photophobia, corneal infiltrates, nausea and decreased vision.

to report suspected adverse reactions call 1-800-332-1088 [to report suspected adverse reactions call 1-800-332-1088]

OVERDOSAGE SECTION

A topical overdose of Ciprofloxacin Ophthalmic Solution may be flushed from the eye(s) with warm tap water.

DOSAGE & ADMINISTRATION SECTION

Corneal Ulcers: The recommended dosage regimen for the treatment of corneal ulcers is two drops into the affected eye every 15 minutes for the first six hours and then two drops into the affected eye every 30 minutes for the remainder of the first day. On the second day, instill two drops in the affected eye hourly. On the third through the fourteenth day, place two drops in the affected eye every four hours. Treatment may be continued after 14 days if corneal re-epithelialization has not occurred.

Bacterial Conjunctivitis: The recommended dosage regimen for the treatment of bacterial conjunctivitis is one or two drops instilled into the conjunctival sac(s) every two hours while awake for two days and one or two drops every four hours while awake for the next five days.

How Supplied: As a sterile ophthalmic solution, in a plastic dispenser:

2.5 mL NDC16571-120-25

5 mL NDC16571-120-50

STORAGE: Store at 25°C (77°F); excursions permitted to15 - 30°C (59 - 86°F) [See USP controlled room temperature]. Protect from light. Retain in carton until contents are used.

ANIMAL PHARMACOLOGY & OR TOXICOLOGY SECTION

Ciprofloxacin and related drugs have been shown to cause arthropathy in immature animals of most species tested following oral administration. However, a one-month topical ocular study using immature Beagle dogs did not demonstrate any articular lesions.

Rx Only

Manufactured in India for:

Nexus Pharmaceuticals Inc.,

Distributed by: Pack Pharmaceuticals, LLC, Buffalo Grove, IL, 60089.

Close